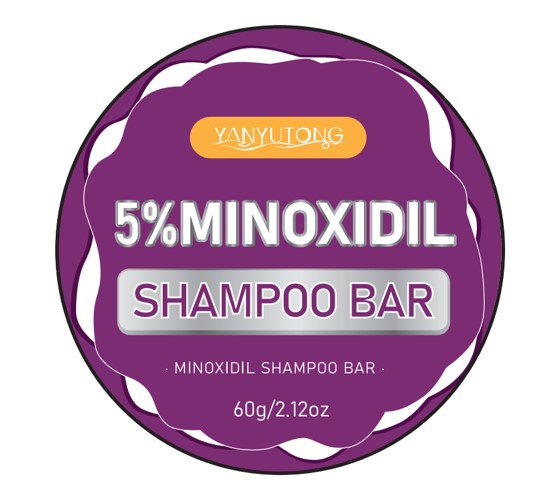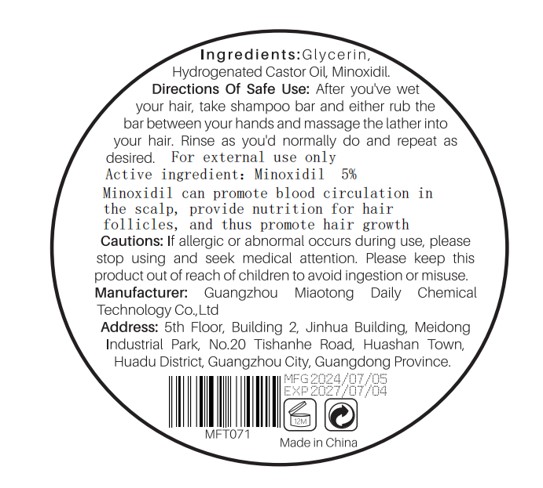 DRUG LABEL: 5% MINOXIDIL SHAMPOOBAR
NDC: 84519-003 | Form: SALVE
Manufacturer: Guangzhou Miaotong Daily Chemical Technology Co., Ltd
Category: otc | Type: HUMAN OTC DRUG LABEL
Date: 20240920

ACTIVE INGREDIENTS: MINOXIDIL 0.05 g/1 g
INACTIVE INGREDIENTS: GLYCERIN; HYDROGENATED CASTOR OIL

5% MINOXIDIL SHAMPOO BAR

ACTIVE INGREDIENT

Minoxidil 5%

PURPOSE

Promote hair growth

Please keep thisproduct out of reach of children

INDICATIONS AND USAGE

Minoxidil can promote blood circulation inthe scalp, provide nutrition for hairfollicles, and thus promote hair growth.

WARNINGS

For external use only.

Cautions: lf allergic or abnormal occurs during use, pleasestop using and seek medical attention. Please keep thisproduct out of reach of children to avoid ingestion or misuse.

DOSAGE AND ADMINISTRATION

Directions Of Safe Use: After you've wetyour hair, take shampoo bar and either rub thebar between your hands and massage the lather intoyour hair. Rinse as you'd normally do and repeat asdesired. For external use only

INACTIVE INGREDIENT

Glycerin
Hydrogenated Castor Oil